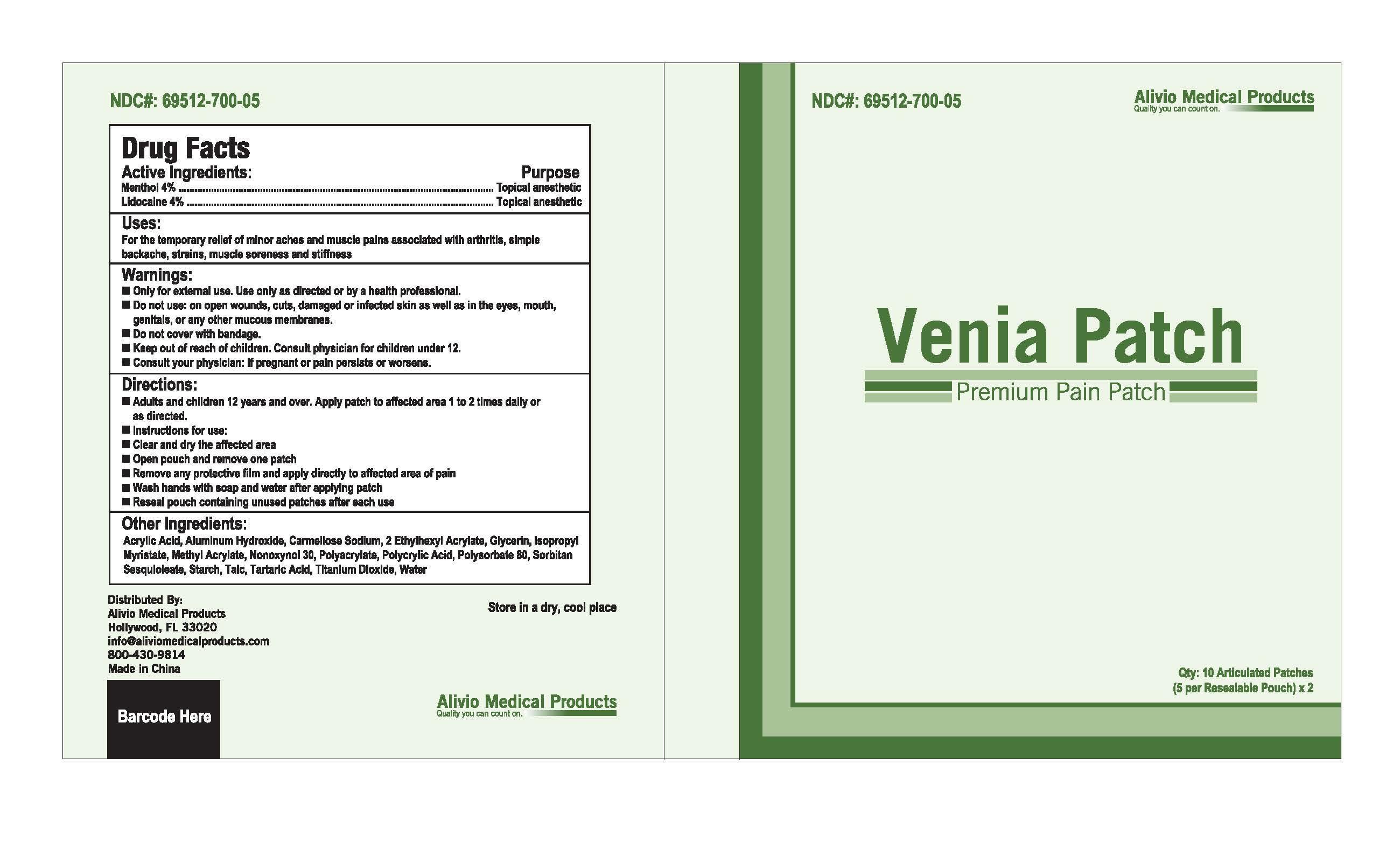 DRUG LABEL: Venia Patch
NDC: 69512-700 | Form: PATCH
Manufacturer: Alivio Medical Products, LLC
Category: otc | Type: HUMAN OTC DRUG LABEL
Date: 20150819

ACTIVE INGREDIENTS: MENTHOL, UNSPECIFIED FORM 4 mg/100 g; LIDOCAINE 4 mg/100 g
INACTIVE INGREDIENTS: ACRYLIC ACID; ALUMINUM HYDROXIDE; CARBOXYMETHYLCELLULOSE SODIUM, UNSPECIFIED FORM; 2-ETHYLHEXYL ACRYLATE; GLYCERIN; ISOPROPYL MYRISTATE; METHYL ACRYLATE; NONOXYNOL-30; POLYACRYLIC ACID (8000 MW); POLYSORBATE 80; SORBITAN SESQUIOLEATE; STARCH, CORN; TALC; TARTARIC ACID; TITANIUM DIOXIDE; WATER

Drug Facts

Active Ingredients

Menthol 4 %

Lidocaine 4 %

Purpose

Topical anesthetic

Topical anesthetic

Uses:

For the temporary relief of minor aches and muscle pains associated with arthritis, simple

backache, strains, muscle soreness and stiffness

Warnings:

-Only for external use. Use only as directed or by a health professional.

-Do not use: on open wounds, cuts, damaged or infected skin as well as in the eyes, mouth,

genitals, or any other mucous membranes.

-Do not cover with bandage.

-Keep out of reach of children.Consult physician for children under 12.

-Consult your physician: if pregnant or pain persists or worsens.

Directions:

-Adults and children 12 years and over. Apply patch to affected area 1 to 2 times daily or

as directed.

-Instructions for use:

-Clear and dry the affected area

-Open pouch and remove one patch

-Remove any protective film and apply directly to affected area of pain

-Wash hands with soap and water after applying patch

-Reseal pouch containing unused patches after each use

Keep out of reach of children. Consult physician for children under 12

INACTIVE INGREDIENT

Other ingredients:

Acrylic Acid, Aluminum Hydroxide, Carmellose Sodium, 2 Ethylhexyl Acrylate, Glycerin, Isopropyl

Myristate, Methyl Acrylate, Nonoxynol 30, Polyacrylate, Polyacrylic Acid, Polysorbate 80, Sorbitan

Sesquioleate, Starch, Talc, Tartaric Acid, Titanium Dioxide, Water